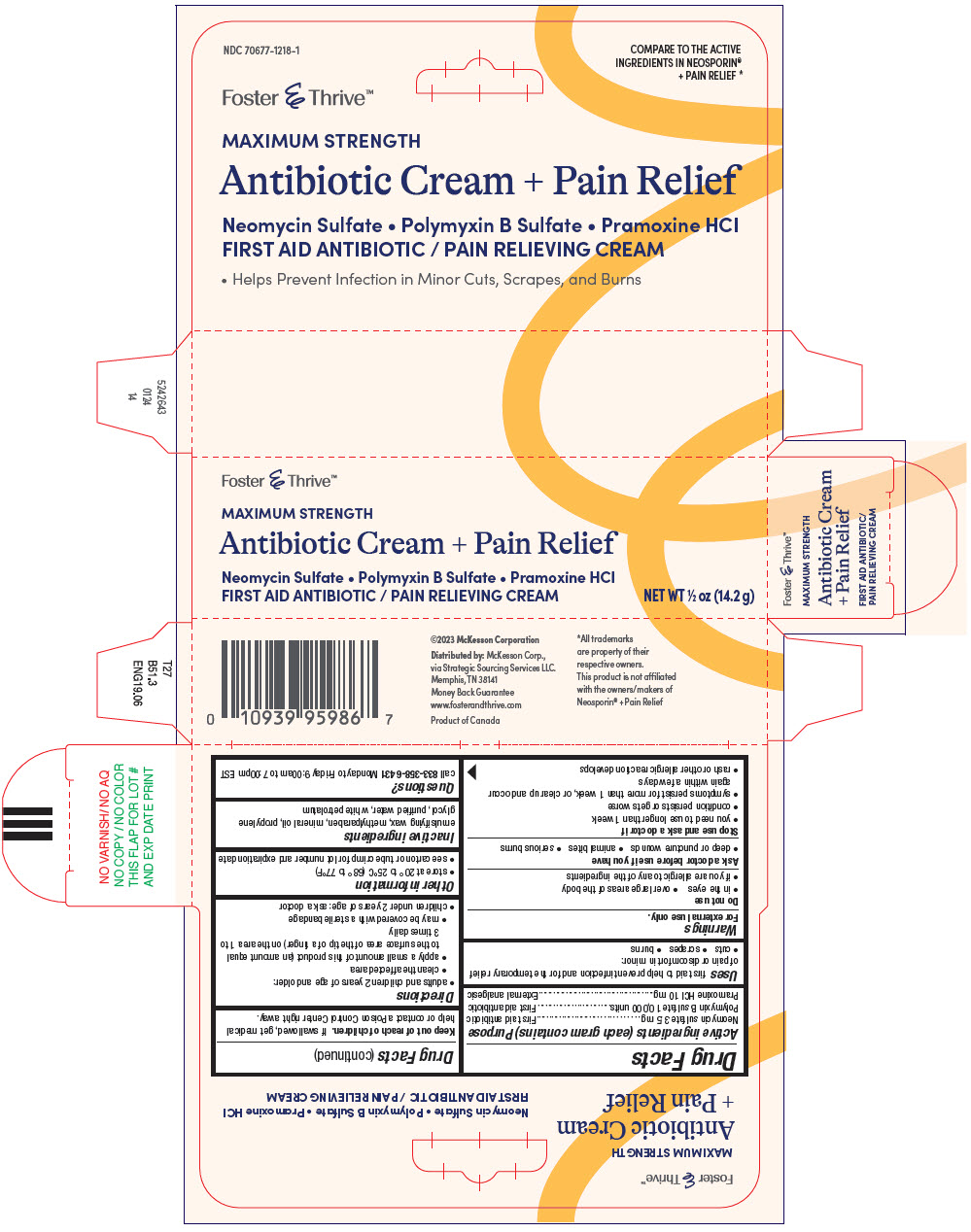 DRUG LABEL: Antibiotic and Pain Relief
NDC: 70677-1218 | Form: CREAM
Manufacturer: STRATEGIC SOURCING SERVICES LLC
Category: otc | Type: HUMAN OTC DRUG LABEL
Date: 20250711

ACTIVE INGREDIENTS: NEOMYCIN SULFATE 3.5 mg/1 g; POLYMYXIN B SULFATE 10000 [USP'U]/1 g; PRAMOXINE HYDROCHLORIDE 10 mg/1 g
INACTIVE INGREDIENTS: METHYLPARABEN; MINERAL OIL; PROPYLENE GLYCOL; WATER; WHITE PETROLATUM

Antibiotic Cream+Pain Relief

Drug Facts

ACTIVE INGREDIENT

Active ingredients (each gram contains) | Purpose
Neomycin sulfate 3.5 mg | First aid antibiotic
Polymyxin B sulfate 10,000 units | First aid antibiotic
Pramoxine HCl 10 mg | External analgesic

Uses

first aid to help prevent infection and for the temporary relief of pain or discomfort in minor:

- cuts
- scrapes
- burns

Warnings

For external use only.

Do not use

- in the eyes
- over large areas of the body
- if you are allergic to any of the ingredients

Ask a doctor before use if you have

- deep or puncture wounds
- animal bites
- serious burns

Stop use and ask a doctor if

- you need to use longer than 1 week
- condition persists or gets worse
- symptoms persist for more than 1 week, or clear up and occur again within a few days
- rash or other allergic reaction develops

Keep out of reach of children.If swallowed, get medical help or contact a Poison Control Center right away.

Directions

- adults and children 2 years of age and older:
  - clean the affected area
  - apply a small amount of this product (an amount equal to the surface area of the tip of a finger) on the area 1 to 3 times daily
  - may be covered with a sterile bandage
- children under 2 years of age: ask a doctor

Other information

- store at 20° to 25°C (68° to 77°F)
- see carton or tube crimp for lot number and expiration date

Inactive ingredients

emulsifying wax, methylparaben, mineral oil, propylene glycol, purified water, white petrolatum

Questions?

call 833-358-6431Monday to Friday 9:00am to 7:00pm EST

Distributed by:McKesson Corp.,
via Strategic Sourcing Services LLC.
Memphis, TN 38141

PRINCIPAL DISPLAY PANEL - 14.2 g Tube Carton

Foster & Thrive™

MAXIMUM STRENGTH
Antibiotic Cream + Pain Relief

Neomycin Sulfate • Polymyxin B Sulfate • Pramoxine HCl
FIRST AID ANTIBIOTIC / PAIN RELIEVING CREAM

NET WT ½ oz (14.2 g)